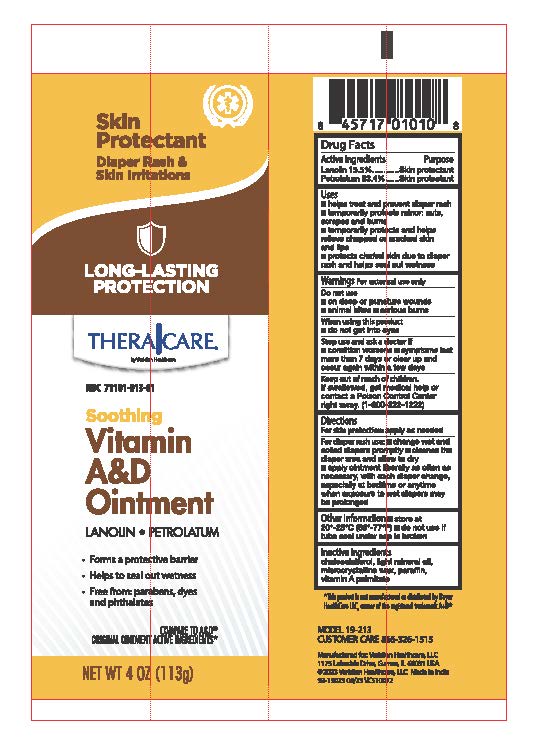 DRUG LABEL: TheraCare A and D
NDC: 71101-013 | Form: OINTMENT
Manufacturer: Veridian Healthcare
Category: otc | Type: HUMAN OTC DRUG LABEL
Date: 20260129

ACTIVE INGREDIENTS: LANOLIN 15.5 g/100 g; PETROLATUM 53.4 g/100 g
INACTIVE INGREDIENTS: PARAFFIN; LIGHT MINERAL OIL; MICROCRYSTALLINE WAX; CHOLECALCIFEROL; VITAMIN A PALMITATE

TheraCare A&D Ointment

Drug Facts

Active ingredients

Lanolin 15.5% .
Petrolatum 53.4% ..

Active ingredients | Purpose
Lanolin 15.5% | Skin Protectant
Petrolatum 53.4% | Skin Protectant

Uses

- helps treat and prevent diaper rash
- temporarily protects minor:
  - cuts
  - scrapes
  - burns
- temporarily protects and helps relieve chapped, chafed or cracked skin and lips
- protect chafed skin due to diaper rash and helps seal out wetness

Warnings

For external use only

Do not use on

- deep or puncture wounds .
- animal bites
- serious burns .

When using this product

- do not get into eyes

Stop use and ask a doctor if

- condition worsens
- symptoms last more than 7 days or clear up and occur again within a few days

Keep out of reach of children. If swallowed, get medical help or contact a Poison Control Center right away. (1-800-222-1222)

Directions

- for skin protectant use apply as needed
- for diaper rash use:
  - change wet and soiled diapers promptly
  - cleanse the diaper area, and allow to dry
  - apply ointment liberally as often as necessary, with each diaper change, especially at bedtime or anytime when exposure to wet diapers may be prolonged

Other information

- store between 20°C to 25 °C (68° to 77°F)
- do not use if tube seal under cap is broken

Inactive Ingredients

cholecalciferol, light mineral oil, microcrystalline wax, paraffin, vitamin A palmitate